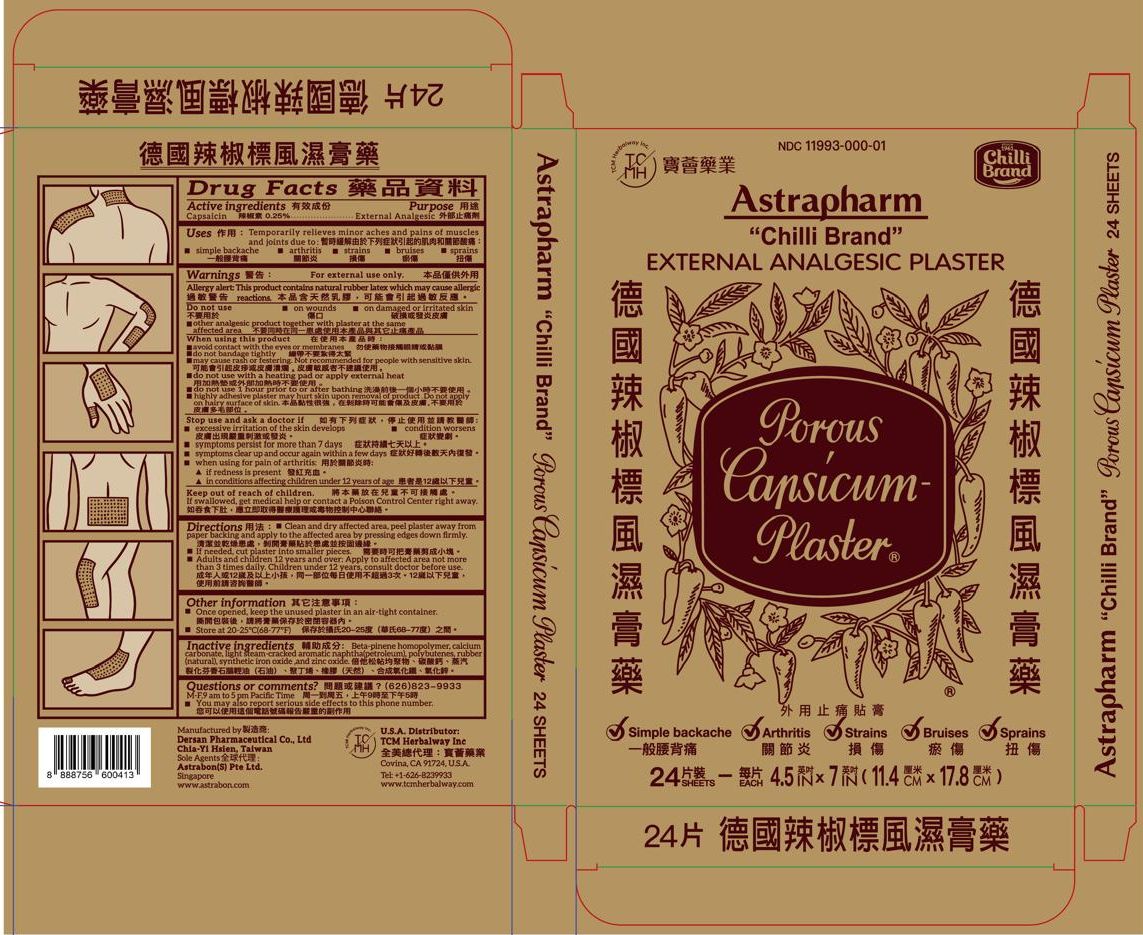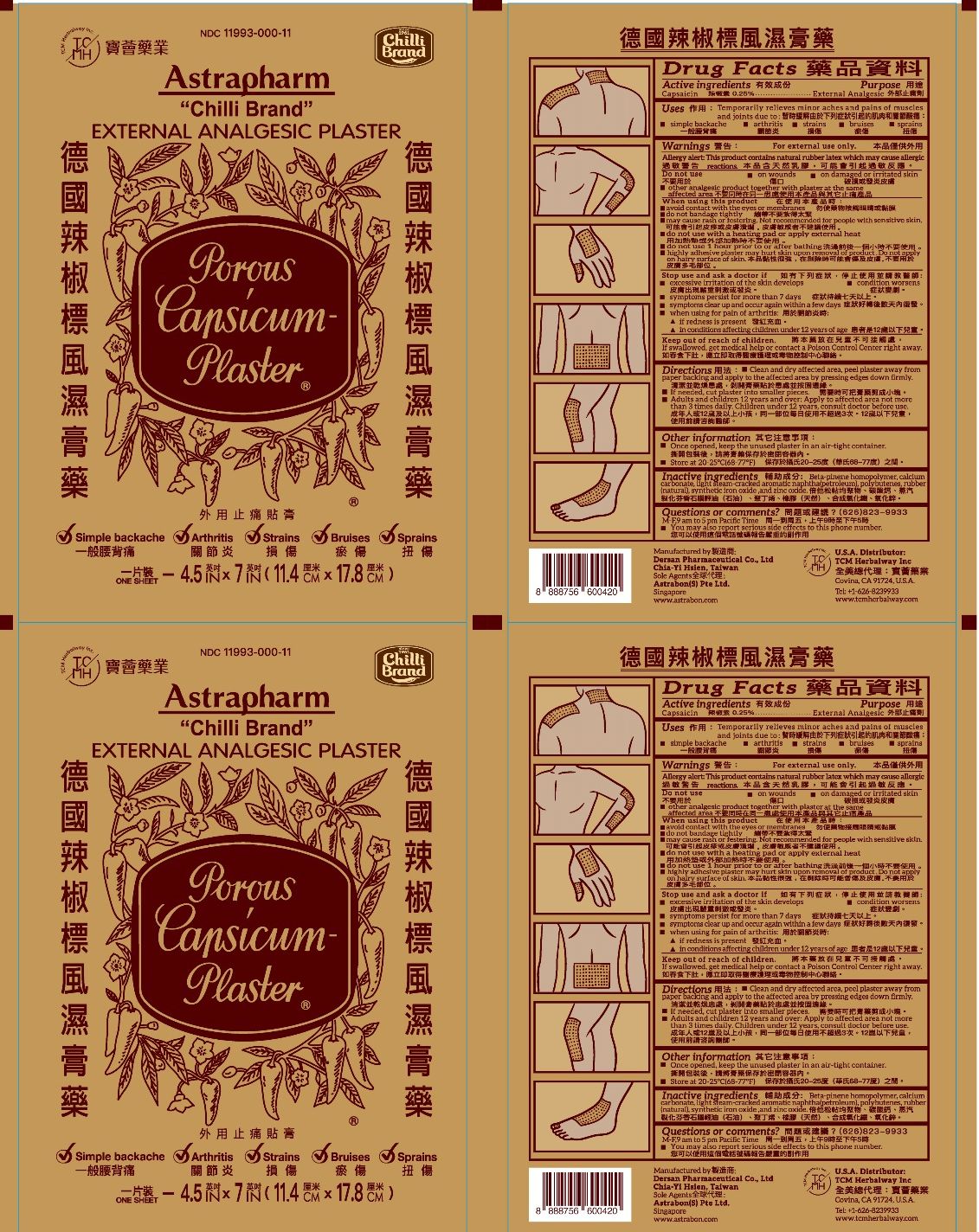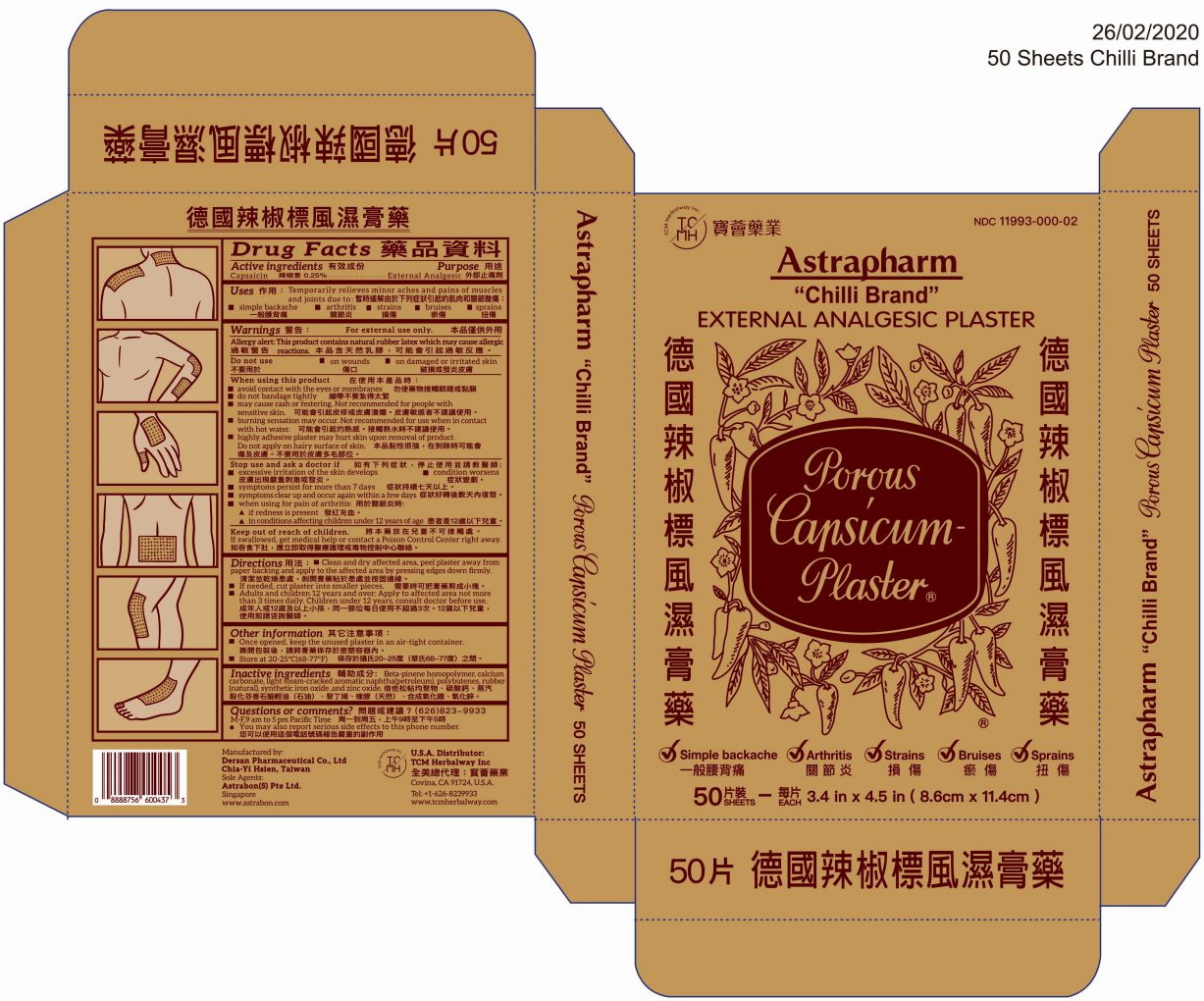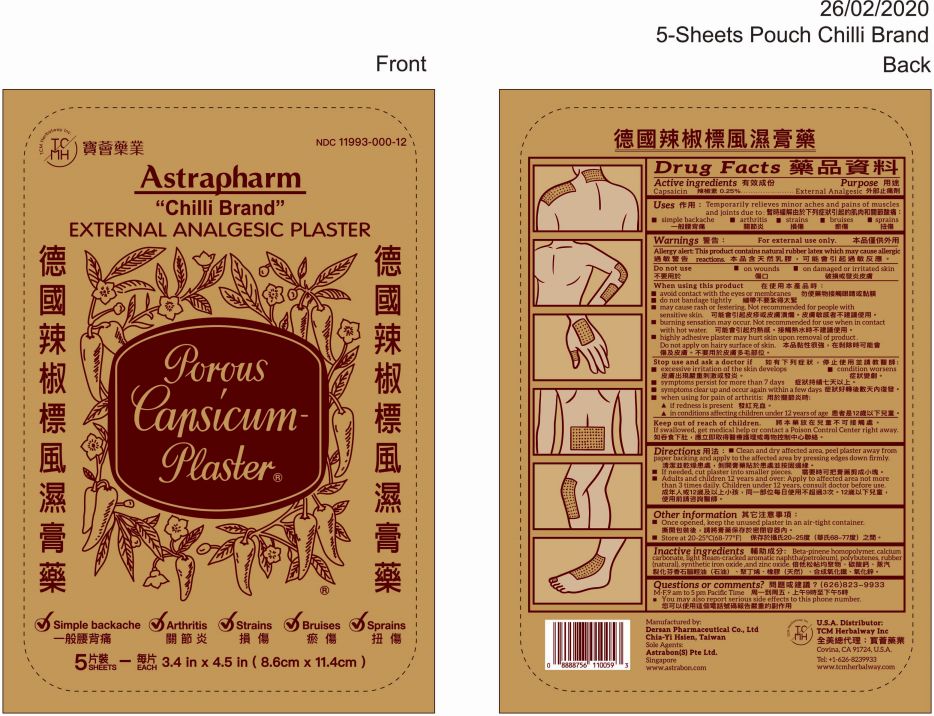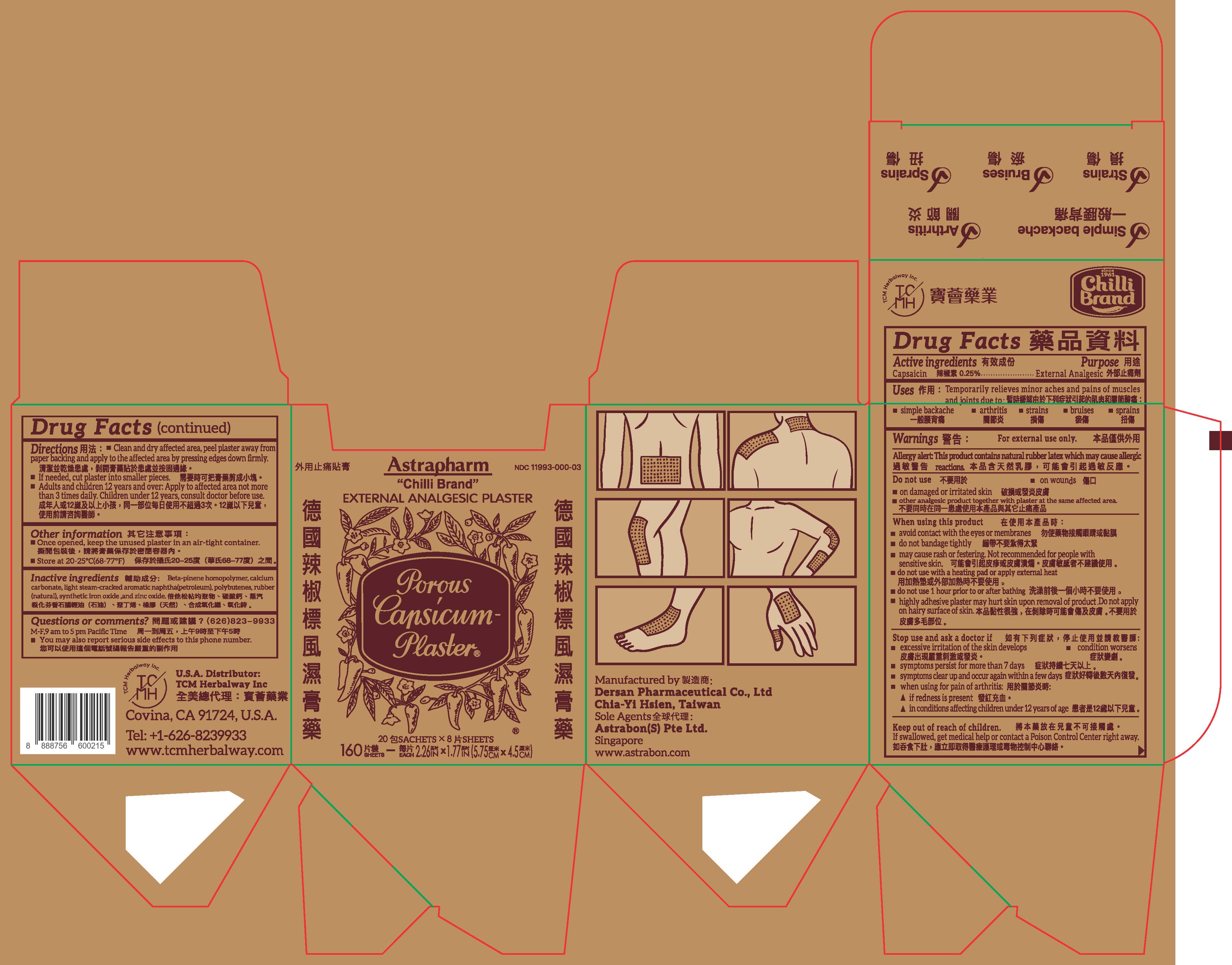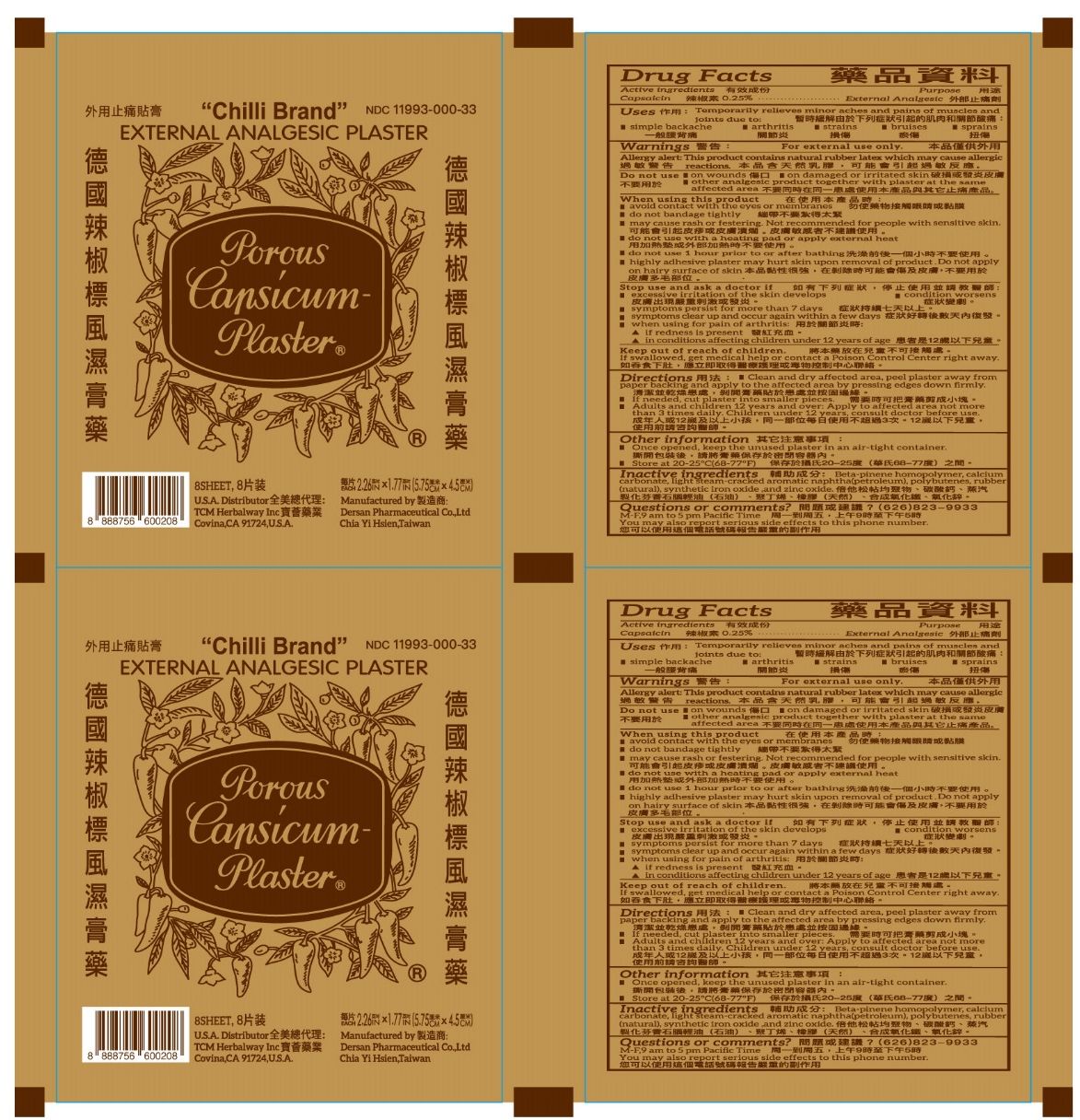 DRUG LABEL: ASTRAPHARM CHILLI BRAND
NDC: 11993-000 | Form: PLASTER
Manufacturer: Dersan Pharmaceutical Co., Ltd
Category: otc | Type: HUMAN OTC DRUG LABEL
Date: 20250110

ACTIVE INGREDIENTS: CAPSAICIN 0.25 g/100 g
INACTIVE INGREDIENTS: .BETA.-PINENE; CALCIUM CARBONATE; NAPHTHA; POLYBUTENE (1400 MW); NATURAL LATEX RUBBER; BROWN IRON OXIDE; ZINC OXIDE

ASTRAPHARM CHILLI BRAND EXTERNAL ANALGESIC PLASTER

Active ingredients

Capsaicin 0.25%..............................External analgesic

Stop use and ask doctor if

Keep out of reach of children

If swallowed, get medical help or contact a Poison Control Center right away.

Directions:

- Clean and dry affected area, peel plaster away from paper backing and apply to the affected area by pressing edges down firmly.
- If needed, cut plaster into smaller pieces.
- Adults and children 12 years of age and over: Apply to affected area not more than 3 times daily. Children under 12 years, consult doctor before use.

Other information:

- Once opened, keep the unused plaster in an air-tight container.
- Store at 20-25°C(68-77°F)

Inactive ingredients:

Beta-pinene homopolymer, calcium carbonate, light steam-cracked aromatic naphtha(petroleum), polybutenes, rubber(natural), synthetic iron oxide, and zinc oxide

Questions or comments?

M-F, 9 am to 5 pm Pacific Time

- You may also report serious side effects to this phone number.

Purpose

External analgesic

Do not use

- on wounds
- damaged or irritated skin

When using this product

- avoid contact with the eyes or mucous membranes
- do not bandage tightly
- may cause rash or festering. Not recommended for people with sensitive skin.
- burning sensation may occur. Not recommended for use when in contact with hot water.
- highly adhesive plaster may hurt skin upon removal of product. Do not apply on hairy surface of skin.

Stop use and ask a doctor if

- Excessive irritation of the skin develops
- Condition worsens
- Symptoms persist for more than 7 days
- Symptoms clear up and occur again within a few days
- When using for pain of arthritis:
- if redness is present
- in conditions affecting children under 12 years of age

Uses:

Temporarily relieves minor aches and pains of muscles and joints due to:

- simple backache
- arthritis
- strains
- bruises
- sprains

Warnings

For external use only